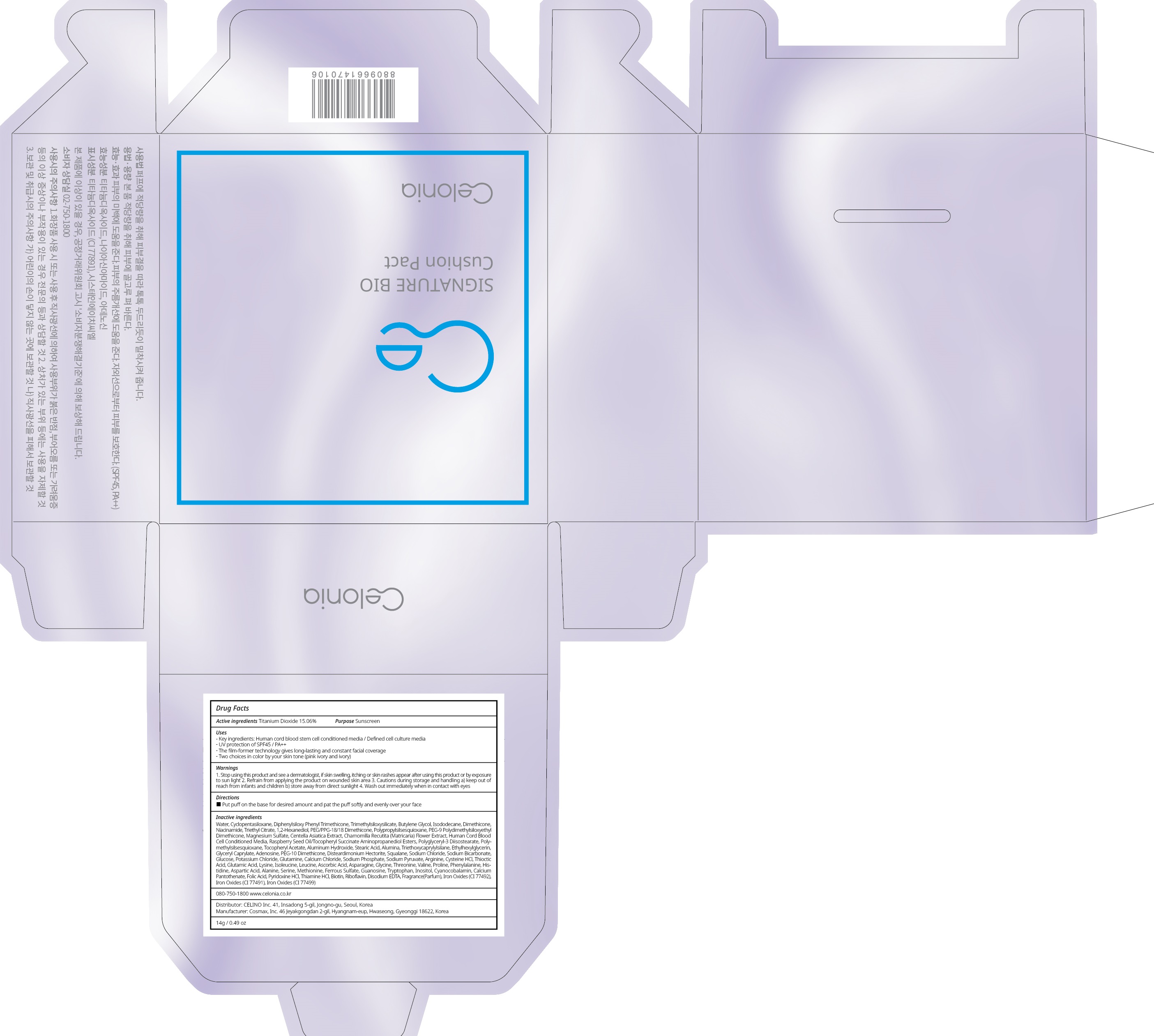 DRUG LABEL: CELONIA SIGNATURE BIO CUSHION PACT PINK IVORY
NDC: 73655-080 | Form: POWDER
Manufacturer: Celino Inc.
Category: otc | Type: HUMAN OTC DRUG LABEL
Date: 20200310

ACTIVE INGREDIENTS: Titanium Dioxide 2.10 g/14 g
INACTIVE INGREDIENTS: Water; CYCLOMETHICONE 5

ACTIVE INGREDIENT

Active ingredients: Titanium Dioxide 15.06%

INACTIVE INGREDIENT

Inactive ingredients:

Water,Cyclopentasiloxane, Diphenylsiloxy Phenyl Trimethicone , Trimethylsiloxysilicate, Butylene Glycol, Isododecane, Dimethicone, Niacinamide , Triethyl Citrate, 1,2-Hexanediol, PEG/PPG-18/18 Dimethicone, Polypropylsilsesquioxane, PEG-9 Polydimethylsiloxyethyl Dimethicone, Magnesium Sulfate, Centella Asiatica Extract, Chamomilla Recutita (Matricaria) Flower Extract, Human Cord Blood Cell Conditioned Media, Raspberry Seed Oil/Tocopheryl Succinate Aminopropanediol Esters, Polyglyceryl-3 Diisostearate, Polymethylsilsesquioxane, Tocopheryl Acetate, Aluminum Hydroxide, Stearic Acid, Alumina, Triethoxycaprylylsilane, Ethylhexylglycerin, Glyceryl Caprylate, Adenosine, PEG-10 Dimethicone, Disteardimonium Hectorite, Squalane, Sodium Chloride, Sodium Bicarbonate, Glucose, Potassium Chloride, Glutamine, Calcium Chloride, Sodium Phosphate, Sodium Pyruvate, Arginine, Cysteine HCl, Thioctic Acid, Glutamic Acid, Lysine, Isoleucine, Leucine, Ascorbic Acid, Asparagine, Glycine, Threonine, Valine, Proline, Phenylalanine, Histidine, Aspartic Acid, Alanine, Serine, Methionine, Ferrous Sulfate, Guanosine, Tryptophan, Inositol, Cyanocobalamin, Calcium Pantothenate, Folic Acid, Pyridoxine HCl, Thiamine HCl, Biotin, Riboflavin, Disodium EDTA, Fragrance(Parfum), Iron Oxides (CI 77492), Iron Oxides (CI 77491), Iron Oxides (CI 77499)

PURPOSE

Purpose: Sunscreen

WARNINGS

1. Stop using this product and see a dermatologist, if skin swelling, itching or skin rashes appear after using this product or by exposure to sun light

2. Refrain from applying the product on wounded skin area

3. Cautions during storage and handling a) keep out of reach from infants and children b) store away from direct sunlight

4. Wash out immediately when in contact with eyes

QUESTIONS

080-750-1800

www.celonia.co.kr

DESCRIPTION

Uses:
Key ingredients: Human cord blood stem cell conditioned media / Defined cell culture media
UV protection of SPF45 / PA++
The film-former technology gives long-lasting and constant facial coverage
Two choices in color by your skin tone (pink ivory and ivory)

Directions: Put puff on the base for desired amount and pat the puff softly and evenly over your face